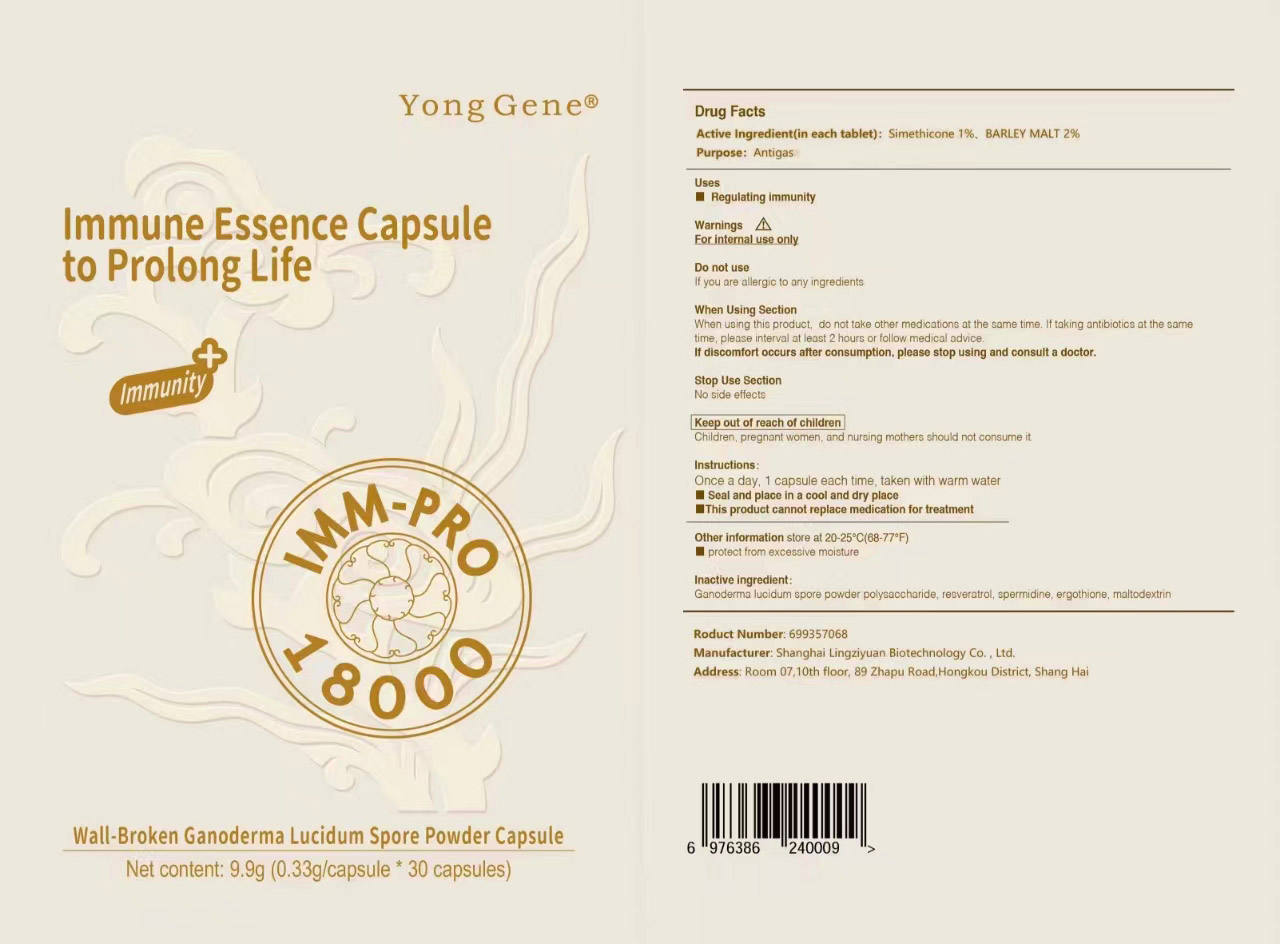 DRUG LABEL: Immune Essence   to Prolong Life
NDC: 83614-001 | Form: CAPSULE
Manufacturer: Shanghai Lingziyuan Biotechnology Co. , Ltd.
Category: otc | Type: HUMAN OTC DRUG LABEL
Date: 20230809

ACTIVE INGREDIENTS: BARLEY MALT 2 g/100 g; DIMETHICONE 1 g/100 g
INACTIVE INGREDIENTS: REISHI; SPERMIDINE; MALTODEXTRIN; RESVERATROL; ERGOTHIONEINE

83614-001

Active Ingredient

Simethicone 1%

BARLEY MALT 2%

Purpose

Antigas

Uses

Regulating immunity

WARNINGS

For internal use only

Do not use

If you are allergic to any ingredients

When Using Section

When using this product , do not take other med cations at the same time . If taking antibiotics at the sametime, please interval at least 2 hours or follow med ical advice.

If discomfort occurs after consumption. please stop using and consult a doctor.

Stop Use Section

No side effects

Keep out of reach of children

Children, pregnant women, and nursing mothers should not consume it

DOSAGE AND ADMINISTRATION

Once a day, 1 capsule each time, taken with warm water
Seal and place in a cool and dry place
This product cannot replace medication for treatment

Other information

store at 20-25°C (68-77°F)
protect from excessive moisture

Inactive ingredient

Ganoderma lucidum spore powder polysaccharide, Resveratrol, Spermidine, Ergothioneine, Maltodextrin